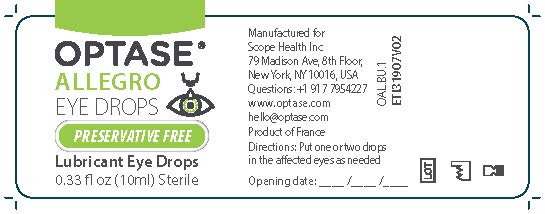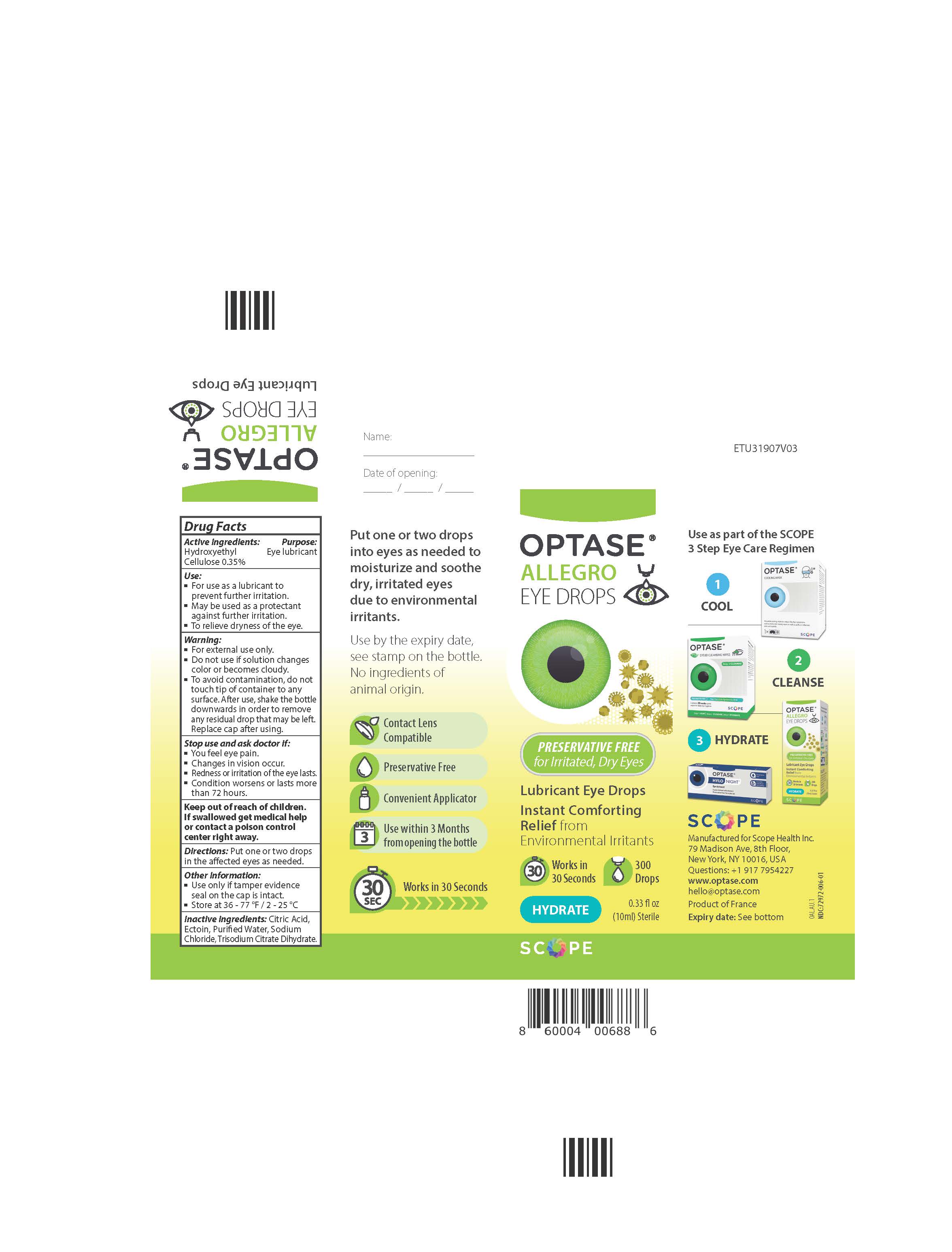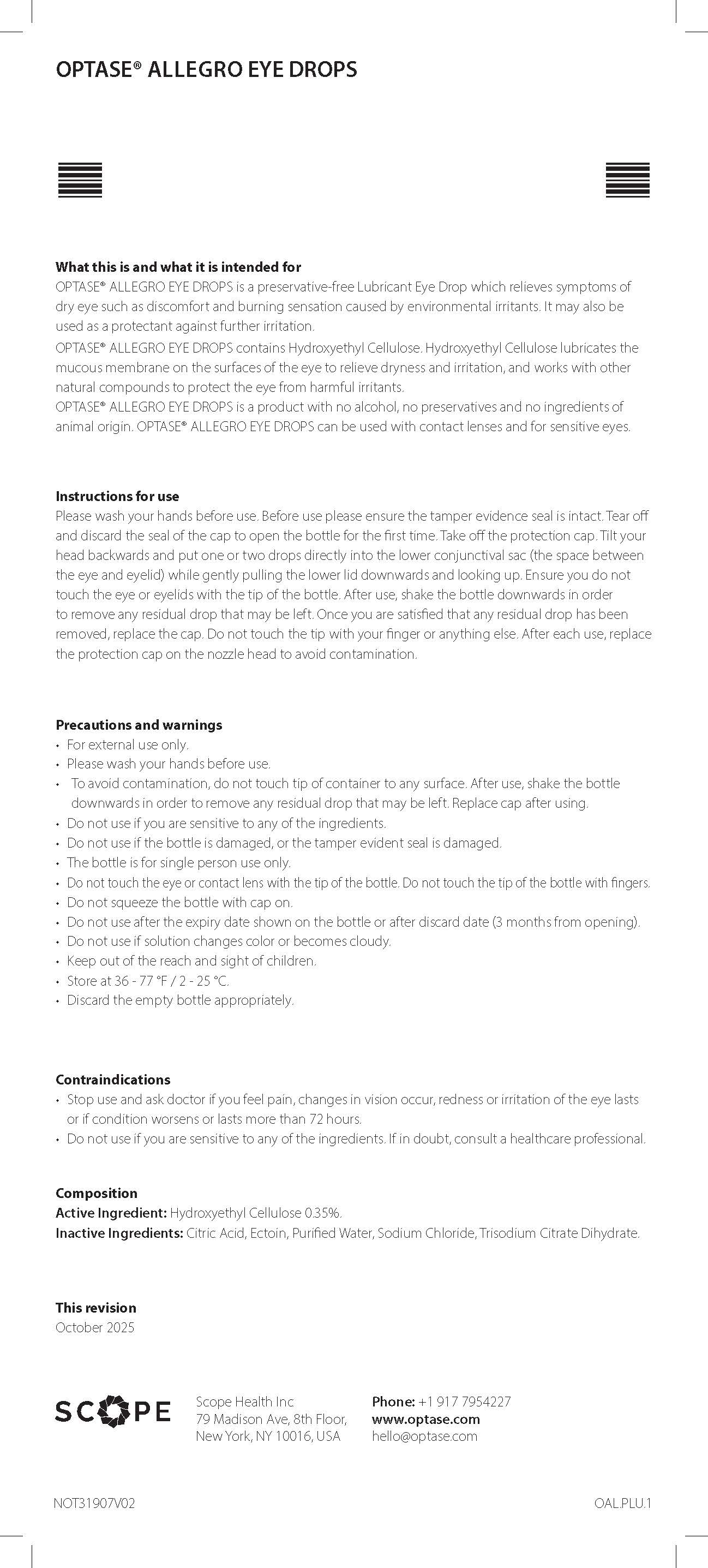 DRUG LABEL: Optase Allegro
NDC: 72972-006 | Form: SOLUTION/ DROPS
Manufacturer: Scope Health Inc
Category: otc | Type: HUMAN OTC DRUG LABEL
Date: 20260127

ACTIVE INGREDIENTS: HYDROXYETHYL CELLULOSE (140 CPS AT 5%) 0.35 mg/1 mL
INACTIVE INGREDIENTS: ECTOINE; SODIUM CHLORIDE; ANHYDROUS CITRIC ACID; TRISODIUM CITRATE DIHYDRATE; WATER

Optase Allegro Eye Drops

ACTIVE INGREDIENT

0.35% Hydroxyethyl Cellulose

Keep out of reach of children.
If swallowed get medical
help or contact a poison
control center right away.

PURPOSE

Eye Lubricant

Inactive ingredients: Citric Acid,
Ectoin, Purified Water, Sodium
Chloride, Trisodium Citrate Dihydrate.

Directions:
Put one or two drops in the
affected eyes as needed.

Warning
• For external use only.
• If solution changes color or
becomes cloudy, do not use.

To avoid contamination, do

not touch tip to any surface.

After use, shake the bottle

downwards in order to remove
any residual drop that may be left.
Replace cap after using.
Stop use and ask doctor if:

Stop use and ask doctor if
• You feel eye pain.
• Changes in vision occur.
• Redness or irritation of the eye lasts.
• Condition worsens or lasts
more than 72 hours

Uses
• For use as a lubricant to prevent
further irritation.
• May be used as a protectant against
further irritation.
• To relieve dryness of the eye.